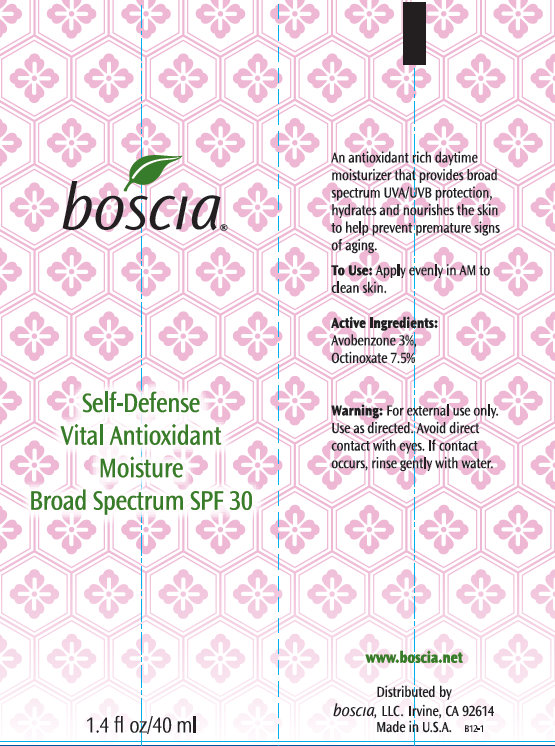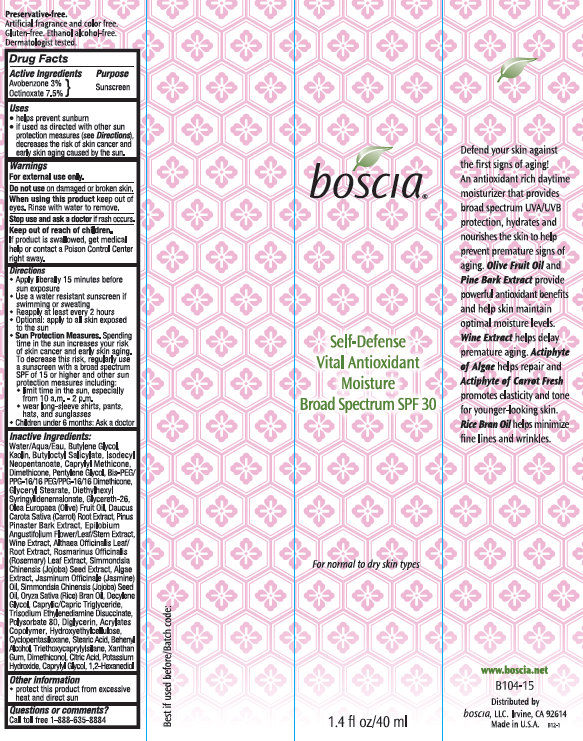 DRUG LABEL: Boscia Self-Defense Vital Antioxidant Moisture Broad Spectrum SPF 30

NDC: 76151-251 | Form: CREAM
Manufacturer: Boscia LLC
Category: otc | Type: HUMAN OTC DRUG LABEL
Date: 20231212

ACTIVE INGREDIENTS: AVOBENZONE 30 mg/1 mL; OCTINOXATE 75 mg/1 mL
INACTIVE INGREDIENTS: WATER; BUTYLENE GLYCOL; KAOLIN; BUTYLOCTYL SALICYLATE; ISODECYL NEOPENTANOATE; CAPRYLYL TRISILOXANE; DIMETHICONE; PENTYLENE GLYCOL; GLYCERYL MONOSTEARATE; DIETHYLHEXYL SYRINGYLIDENEMALONATE; GLYCERETH-26; OLIVE OIL; CARROT; MARITIME PINE; EPILOBIUM ANGUSTIFOLIUM LEAF; ALTHAEA OFFICINALIS LEAF; ROSEMARY; SIMMONDSIA CHINENSIS SEED; JASMINUM OFFICINALE FLOWER; JOJOBA OIL; RICE BRAN OIL; DECYLENE GLYCOL; MEDIUM-CHAIN TRIGLYCERIDES; TRISODIUM ETHYLENEDIAMINE DISUCCINATE; POLYSORBATE 80; DIGLYCERIN; CYCLOMETHICONE 5; STEARIC ACID; DOCOSANOL; TRIETHOXYCAPRYLYLSILANE; XANTHAN GUM; CITRIC ACID MONOHYDRATE; POTASSIUM HYDROXIDE; CAPRYLYL GLYCOL; 1,2-HEXANEDIOL

Boscia Self-Defense Vital Antioxidant Moisture Broad Spectrum SPF 30

Active ingredients

Avobenzone 3% Octinoxate 7.5%

Purpose

Sunscreen

Uses

- helps prevent sunburn
- if used as directed with other sun protection measures (see), decreases the risk of skin cancer and early skin aging caused by the sun. Directions

Warnings

For external use only.

Do not use

on damaged or broken skin.

When using this product

keep out of eyes. Rinse with water to remove.

Stop use and ask a doctor

if rash occurs.

Keep out of reach of children.

If product is swallowed, get medical help or contact a Poison Control Center right away.

Directions

- Apply liberally 15 minutes before sun exposure
- Use a water resistant sunscreen if swimming or sweating
- Reapply at least every 2 hours
- Optional: apply to all skin exposed to the sun
- Spending time in the sun increases your risk of skin cancer and early skin aging. To decrease this risk regularly use a sunscreen with a broadspectrum SPF of 15 or higher and another sun protection measures including: Sun Protection Measures.
- Limit time in the usn, especially from 10 a.m. - 2 p.m.
- wear long-sleeve shirts, pants, hats, and sunglasses.
- Children under 6 months: Ask a doctor

Inactive Ingredients:

Water/Aqua/Eau, Butylene Glycol, Kaolin, Butyloctyl Salicylate, Isodecyl Neopentanoate, Caprylyl Trisiloxane, Dimethicone, Pentylene Glycol, Bis-PEG/PPG-16/18 PEG/PPG-16/16 Dimethicone, Glyceryl Stearate, Diethylhexyl Syringylidenemalonate, Glycereth-26, Olea Europaea (Olive) Fruit Oil, Daucus Carota Sativa (Carrot) Root Extract, Pinus Pinaster Bark Extract, Epilobium Angustifolium Leaf/Stem Extract, Althaea Officinalis Leaf/Root Extract, Simmondsia Chinensis (Jojoba) Seed Extract, Algae Extract, Jasminum Officinale (Jasmine) Oil, Simmondsia Chinensis (Jojoba) Seed Oil, Oryza Sativa (Rice) Bran Oil, Decylene Glycol, Caprylic/Capric Triglyceride, Trisodium Ethylenediamine Disuccinate, Polysorbate 80, Diglycerin, Acrylates Copolymer, Hydroxyethylcellulose, Cyclopentasiloxane, Behenyl Alcohol, Triethoxycaprylylsilane, Xanthan Gum, Dimethiconol, Citric Acid, Potassium Hydroxide, Caprylyl Glycol, 1,2-Hexanediol

Other Information

- Protect this product from excessive heat and direct sun

Questions or comments?

Call toll free 1-888-635-8884

Boscia Self-Defence Vital Antioxidant Moisture

Defend your skin against the first signs of aging! An antioxidant rich daytime moisturizer that provides broad spectrum UVA/UVB protection, hydrates and nourishes the skin to help prevent premature signs of aging. Olive Fruit Oil and Pine Bark Extract provide powerful antioxidant benefits and help skin maintain optimal moisture levels. Wine Extract helps delay premature aging. Actiphyte of Algaehelps repair and Actiphyte of Carrot Fresh promotes elasticity and tone for younger-looking skin. Rice Bran Oil helps minimize fine lines and wrinkles.

PACKAGE LABEL

boscia Self-Defense Vital Antioxidant Moisture Broad Spectrum SPF 30 1.4 fl oz / 40 ml www.boscia.net B104-15 Distributed by boscia, LLC. Irvine, CA 92614 Made in USA For normal to dry skin types